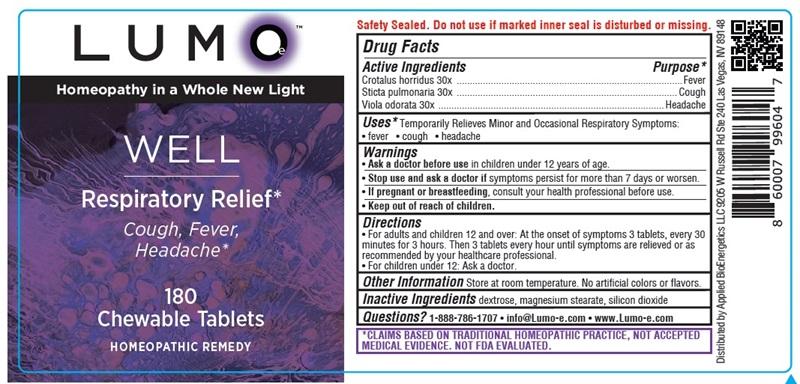 DRUG LABEL: LUMOe WELL Respiratory Relief
NDC: 81425-005 | Form: TABLET, CHEWABLE
Manufacturer: Applied Bioenergetics, LLC
Category: homeopathic | Type: HUMAN OTC DRUG LABEL
Date: 20251110

ACTIVE INGREDIENTS: CROTALUS HORRIDUS HORRIDUS VENOM 30 [hp_X]/1 1; LOBARIA PULMONARIA 30 [hp_X]/1 1; VIOLA ODORATA 30 [hp_X]/1 1
INACTIVE INGREDIENTS: DEXTROSE; MAGNESIUM STEARATE; SILICON DIOXIDE

LUMOe WELL Respiratory Relief

Drug Facts

Active Ingredients
Crotalus horridus 30x
Sticta pulmonaria 30x
Viola odorata 30x

Purpose*
Crotalus horridus ......................................................................................Fever
Sticta pulmonaria .................................................................................... Cough
Viola odorata ...................................................................................... Headache

INDICATIONS AND USAGE

Uses* Temporarily Relieves Minor and Occasional Respiratory Symptoms:
• fever • cough • headache

Warnings
• Ask a doctor before use in children under 12 years of age.
• Stop use and ask a doctor if symptoms persist for more than 7 days or worsen.
• If pregnant or breastfeeding, consult your health professional before use.

• Keep out of reach of children.

Directions
• For adults and children 12 and over: At the onset of symptoms 3 tablets, every 30
minutes for 3 hours. Then 3 tablets every hour until symptoms are relieved or as
recommended by your healthcare professional.
• For children under 12: Ask a doctor.

Other Information Store at room temperature. No artificial colors or flavors.

Inactive Ingredients dextrose, magnesium stearate, silicon dioxide

QUESTIONS

Questions? 1-888-786-1707 • info@Lumo-e.com • www.Lumo-e.com

*CLAIMS BASED ON TRADITIONAL HOMEOPATHIC PRACTICE, NOT ACCEPTED
MEDICAL EVIDENCE. NOT FDA EVALUATED.

LUMOe WELL Respiratory Relief Labelimg

LUMOe
Homeopathy in a Whole New Light

WELL
Respiratory Relief*
Cough, Fever,
Headache*

180
Chewable Tablets
HOMEOPATHIC REMEDY

Distributed by Applied BioEnergetics LLC 9205 W Russell Rd Ste 240 Las Vegas, NV 89148

res